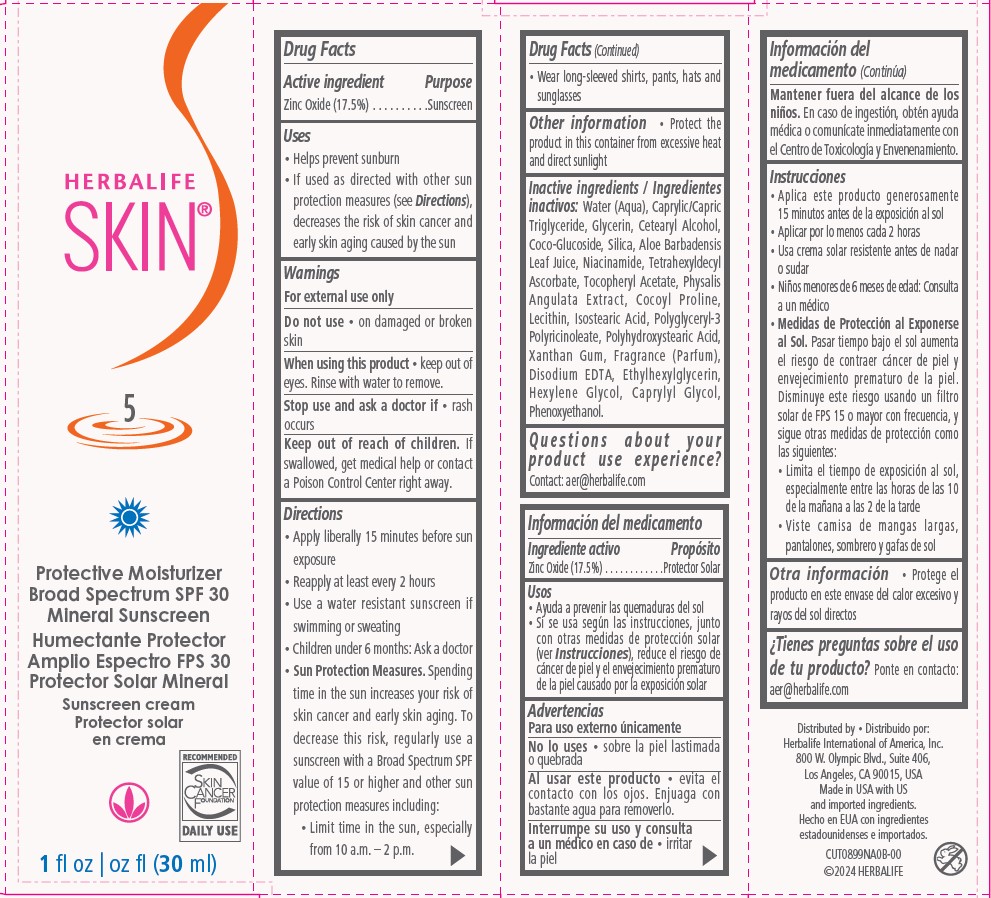 DRUG LABEL: Herbalife SKIN Protective Moisturizer Broad Spectrum SPF 30 Mineral Sunscreen
NDC: 51785-900 | Form: CREAM
Manufacturer: Herbalife International of America Inc.
Category: otc | Type: HUMAN OTC DRUG LABEL
Date: 20250121

ACTIVE INGREDIENTS: ZINC OXIDE 17.5 g/100 mL
INACTIVE INGREDIENTS: EDETATE DISODIUM; WATER; CAPRYLYL GLYCOL; COCO GLUCOSIDE; SILICON DIOXIDE; HEXYLENE GLYCOL; ISOSTEARIC ACID; GLYCERIN; ETHYLHEXYLGLYCERIN; PHYSALIS ANGULATA; NIACINAMIDE; ALOE VERA LEAF; CETOSTEARYL ALCOHOL; COCOYL PROLINE; TETRAHEXYLDECYL ASCORBATE; PHENOXYETHANOL; ALPHA-TOCOPHEROL ACETATE; LECITHIN, SUNFLOWER; POLYHYDROXYSTEARIC ACID (2300 MW); POLYGLYCERYL-3 RICINOLEATE; MEDIUM-CHAIN TRIGLYCERIDES; XANTHAN GUM

Herbalife SKIN Protective Moisturizer Broad Spectrum SPF 30 Mineral Sunscreen

Drug Facts

Purpose

Sunscreen

Active ingredient

Zinc Oxide (17.5%)

Uses
• Helps prevent sunburn
• If used as directed with other sun
protection measures (see Directions),
decreases the risk of skin cancer and
early skin aging caused by the sun

Warnings
For external use only

Do not use • on damaged or broken
skin

When using this product • keep out of
eyes. Rinse with water to remove.

Stop use and ask a doctor if • rash
occurs

Keep out of reach of children. If
swallowed, get medical help or contact
a Poison Control Center right away.

Directions
• Apply liberally 15 minutes before sun
exposure
• Reapply at least every 2 hours
• Use a water resistant sunscreen if
swimming or sweating
• Children under 6 months: Ask a doctor
• Sun Protection Measures. Spending
time in the sun increases your risk of
skin cancer and early skin aging. To
decrease this risk, regularly use a
sunscreen with a Broad Spectrum SPF
value of 15 or higher and other sun
protection measures including:
• Limit time in the sun, especially
from 10 a.m. – 2 p.m.

• Wear long-sleeved shirts, pants, hats and

sunglasses

Other information

• Protect the
product in this container from excessive heat
and direct sunlight

Inactive ingredients:

Water (Aqua), Caprylic/Capric
Triglyceride, Glycerin, Cetearyl Alcohol,
Coco-Glucoside, Silica, Aloe Barbadensis
Leaf Juice, Niacinamide, Tetrahexyldecyl
Ascorbate, Tocopheryl Acetate, Physalis
Angulata Extract, Cocoyl Proline,
Lecithin, Isostearic Acid, Polyglyceryl-3
Polyricinoleate, Polyhydroxystearic Acid,
Xanthan Gum, Fragrance (Parfum),
Disodium EDTA, Ethylhexylglycerin,
Hexylene Glycol, Caprylyl Glycol,
Phenoxyethanol.

Questions about your product use experience?

Contact: aer@herbalife.com

Distributed by:
Herbalife International of America, Inc.
800 W. Olympic Blvd., Suite 406,
Los Angeles, CA 90015, USA
Made in USA with US
and imported ingredients.

CUT0899NA0B-00

©2024 HERBALIFE

PACKAGE LABEL

HERBALIFE

SKIN

5

Protective Moisturizer
Broad Spectrum SPF 30
Mineral Sunscreen

Sunscreen cream

1 fl oz (30 ml)